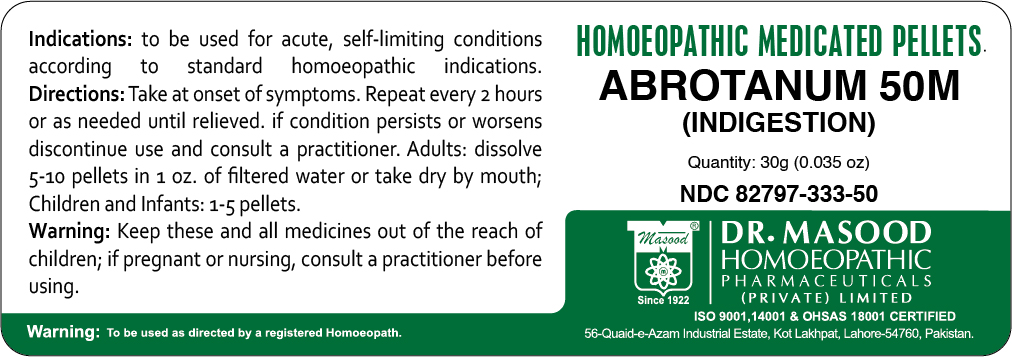 DRUG LABEL: Masood Abrotanum
NDC: 82797-333 | Form: PELLET
Manufacturer: Dr. Masood Homeopathic Pharmaceuticals Private Limited
Category: homeopathic | Type: HUMAN OTC DRUG LABEL
Date: 20230123

ACTIVE INGREDIENTS: ARTEMISIA ABROTANUM FLOWERING TOP 1 g/30 g
INACTIVE INGREDIENTS: LACTOSE, UNSPECIFIED FORM 9 g/30 g

Masood Abrotanum

Dosage and Administartion

- Take at onset of symptoms.
- Repeat every 2 hours or as needed until relieved.
- If conditions persists or worsens discontinue use and consult a practitioner.

Adults: dissolve 5-10 pellets in 1 oz. of filtered water or take dry by mouth

Children and Infants: 1-5 pellets

Indications and Usage

To be used for acute, self-limiting conditions according to standard homeopathic indications

Inactive Ingredient

Lactose

ACTIVE INGREDIENT

Artemisia Abrotanum

Keep out of the reach of children

PURPOSE

To be used for acute, self-limiting conditions according to standard homeopathic indications such as Indigestion

Warnings

Keep these and all medicines out of the reach of children;

if pregnant or nursing consult a practitioner before using.